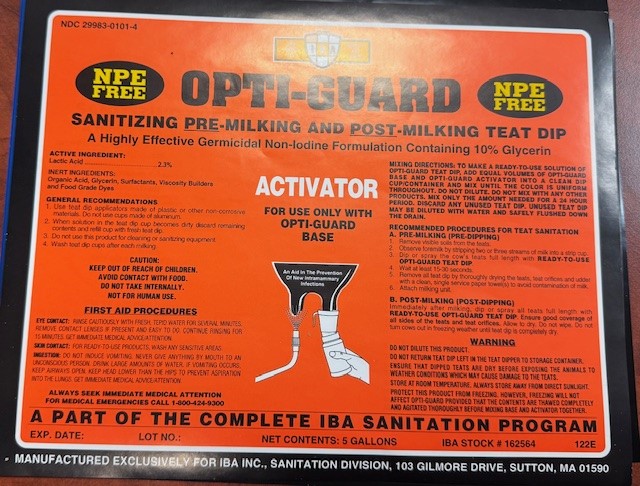 DRUG LABEL: OPTI-GUARD ACTIVATOR
NDC: 29983-0101 | Form: SOLUTION
Manufacturer: IBA
Category: animal | Type: OTC ANIMAL DRUG LABEL
Date: 20241226

ACTIVE INGREDIENTS: LACTIC ACID 23.0 g/1 L
INACTIVE INGREDIENTS: UREA

OPTI-GUARD SANITIZING PRE-MILKING AND POST MILKING TEAT DIP A HIGHLY EFFECTIVE GERMICIDAL NON-IODINE FOMRULATION CONTAINING 10% GLYCERIN

ACTIVE INGREDIENT

LACTIC ACID...........2.3%

INERT INGREDIENTS
Organic Acid, Glycerin, Surfactants Viscosity Builders and Food Grade Dye

INDICATIONS AND USAGE

GENERAL RECOMMENDATIONS

To make an RTU solution of Opti-Guard teat dip, add equal volumes of Opti-Guard Base and Opti-Guard Activator into a clean dip cup/container and mix until the color is uniform throughout. Do not dilute. Do not mix with any other products. Mix only the amount needed for a 24 hour period. Discard any unused teat dip. Unused teat dip may be diluted with water and safely flushed down the drain.

RECOMMENDED PROCEDURES FOR TEAT SANITATION
A. PRE-MILKING (PRE-DIPPING)
1. REMOVE VISIBLE SOILS FROM THE TEATS.
2. OBSERVE FOREMILK BY STRIPPING TWO OR THREE STREAMS OF MILK INTO A STRIP CUP.
3. DIP OR SPRAY THE COW'S TEATS FULL LENGTH WITH READY-TO-USE OPTI-GUARD TEAT DIP.
4 WAIT APPROXIMATELY 30 SECONDS.
5. REMOVE ALL TEAT DIP BY THOROUGHLY DRYING THE TEATS AND TEAT ORIFICES AND UDDER (IF SPRAYING), WITH A CLEAN, SINGLE SERVICE PAPER TOWEL(S).
6. ATTACH MILKING UNIT
B. POST-MILKING(POST DIPPING)

Immediately after milking, dip or spray all teats full length with READY-TO-USE OPTI-GUARD TEAT DIP. Ensure good coverage of all sides of the teats and teat orifices. Allow to dry. Do not wipe. Do not trun cows out in freezing weather until teat dip is completely dry.

WARNING

Do not dilute this product.

Do not return teat dip left in the teat dipper to storage container.

Ensure that dipped teats are dry before exposing the animals to weather conditions which may cause damage to the teats.

Store at room temperature. Always store away from direct sunlight.

Protect this product from freezing. However, freezing will not affect Opti-Guard provided that the contents are thawed completely and agitated thoroughly before mixing base and activator together.

CAUTION: KEEP OUT OF REACH OF CHILDREN.
AVOID CONTACT WITH FOOD. DO NOT TAKE INTERNALLY.

FIRST AID PROCEDURES

EYE CONTACT: Rinse cautiously with fresh, tepid water for several minutes. Remove contact lenses if present and easy to do. Continue rinsing for 15 minutes. Get immediate medical advice/attention. SKIN CONTACT: For RTU products wash any sensitive areas. INGESTION: Do not induce vomiting. Never give anything by mouth to an unconscious person. Drink large amounts of water. If vomiting occurs, keep airways open. Keep head lower than the hips to prevent aspiration into the lungs. Get immediate medical advice/attention.

ALWAYS SEEK IMMEDIATE MEDICAL ATTENTION

FOR MEDICAL EMERGENCIES CALL 1-800-424-9300